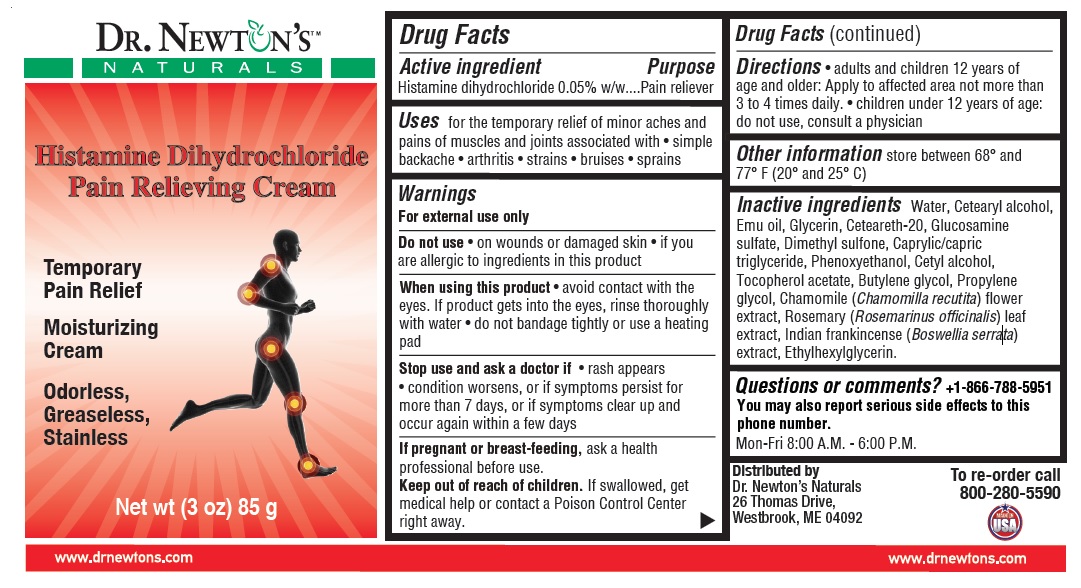 DRUG LABEL: Pain Relieving Cream
NDC: 85063-101 | Form: CREAM
Manufacturer: Mediapower, Inc. DBA Dr Newton's And Naturals
Category: otc | Type: HUMAN OTC DRUG LABEL
Date: 20250219

ACTIVE INGREDIENTS: HISTAMINE DIHYDROCHLORIDE 0.05 g/100 g
INACTIVE INGREDIENTS: WATER; CETOSTEARYL ALCOHOL; EMU OIL; GLYCERIN; POLYOXYL 20 CETOSTEARYL ETHER; GLUCOSAMINE SULFATE; DIMETHYL SULFONE; MEDIUM-CHAIN TRIGLYCERIDES; PHENOXYETHANOL; CETYL ALCOHOL; .ALPHA.-TOCOPHEROL ACETATE; BUTYLENE GLYCOL; PROPYLENE GLYCOL; CHAMOMILE; ROSEMARY; INDIAN FRANKINCENSE; ETHYLHEXYLGLYCERIN

Histamine Dihydrochloride Pain Relieving Cream

Active ingredient

Histamine dihydrochloride 0.05% w/w

Purpose

Pain reliever

Uses

for the temporary relief of minor aches and pains of muscles and joints associated with • simple backache • arthritis • strains • bruises • sprains

Warnings

For external use only

Do not use • on wounds or damaged skin • if you are allergic to ingredients in this product

When using this product • avoid contact with the eyes. If product gets into the eyes, rinse thoroughly with water • do not bandage tightly or use a heating pad

Stop use and ask a doctor if • rash appears • condition worsens, or if symptoms persist for more than 7 days, or if symptoms clear up and occur again within a few days

If pregnant or breastfeeding, ask a health professional before use.

Keep out of reach of children. If swallowed, get medical help or contact a Poison Control Center right away.

Directions

• adults and children 12 years of age and older: Apply to affected area not more than 3 to 4 times daily • children under 12 years of age: do not use, consult a physician

Other information

store between 68° and 77° F (20° and 25° C)

Inactive ingredients:

Water, Cetearyl alcohol, Emu oil, Glycerin, Ceteareth-20, Glucosamine sulfate, Dimethyl sulfone, Caprylic/capric triglyceride, Phenoxyethanol, Cetyl alcohol, Tocopherol acetate, Butylene glycol, Propylene glycol, Chamomile (Chamomilla recutita) flower extract, Rosemary (Rosemarinusofficinalis) leaf extract, Indian frankincense (Boswellia serrata) extract, Ethylhexylglycerin.

Questions or comments?

+1-866-788-5951

You may also report serious side effects to this phone number.

Mon-Fri 8:00 A.M. - 6:00 P.M.

DR. NEWTON'S™ NATURALS

Temporary Pain Relief

Moisturizing Cream

Odorless, Greaseless, Stainless

Distributed by
Dr. Newton's Naturals
26 Thomas Drive,
Westbrook, ME 04092

To re-order call 800-280-5590

MADE IN USA

www.drnewtons.com